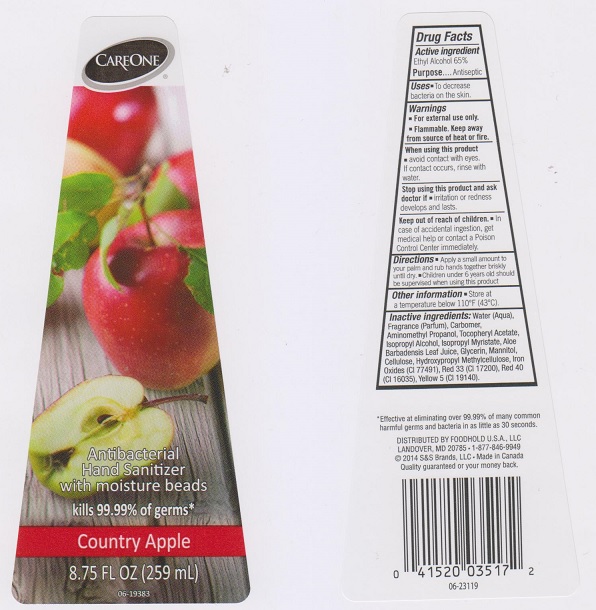 DRUG LABEL: CareOne
NDC: 41520-410 | Form: LIQUID
Manufacturer: American Sales Company
Category: otc | Type: HUMAN OTC DRUG LABEL
Date: 20170517

ACTIVE INGREDIENTS: ALCOHOL 650 mg/1 mL
INACTIVE INGREDIENTS: WATER; CARBOMER 934; AMINOMETHYLPROPANOL; .ALPHA.-TOCOPHEROL ACETATE, DL-; ISOPROPYL ALCOHOL; ISOPROPYL MYRISTATE; ALOE VERA LEAF; GLYCERIN; MANNITOL; POWDERED CELLULOSE; HYPROMELLOSES; FERRIC OXIDE RED; D&C RED NO. 33; FD&C RED NO. 40; FD&C YELLOW NO. 5

Active ingredient

Ethyl Alcohol 65%

Purpose

Antiseptic

Uses

- to decrease bacteria on the skin.

Warnings

- For external use only
- Flammable. Keep away from source of heat or fire

When using this product

- avoid contact with eyes. If contact occurs, rinse with water.

Stop using this product and ask doctor if

- irritation or redness develops and lasts.

Keep out of reach of children.

- In case of accidental ingestion, get medical help or contact a Poison Control Center immediately.

Directions

- apply a small amount to your palm and rub hands together briskly until dry.
- children under 6 years old should be supervised when using this product.

Other information

- store at a room temperature below 110°F (43°C)

Inactive ingredients

Water (Aqua), Fragrance (Parfum), Carbomer, Aminomethyl Propanol, Tocopheryl Acetate, Isopropyl Alcohol, Isopropyl Myristate, Aloe Barbadensis Leaf Juice, Glycerin, Mannitol, Cellulose, Hydroxypropyl Methylcellulose, Iron Oxides (CI 77491), Red 33 (CI 17200), Red 40 (CI 16035), Yellow 5 (CI 19140).